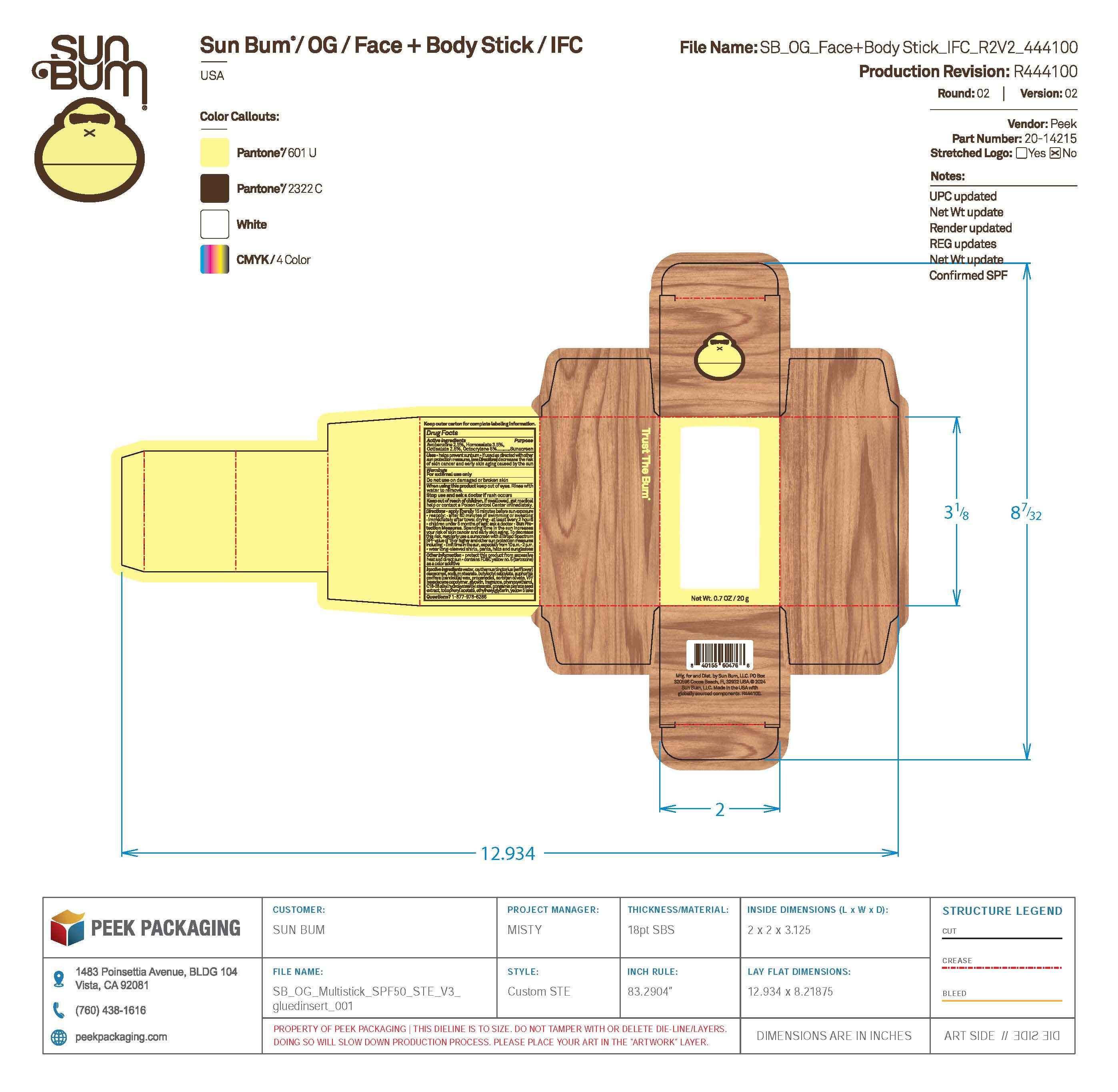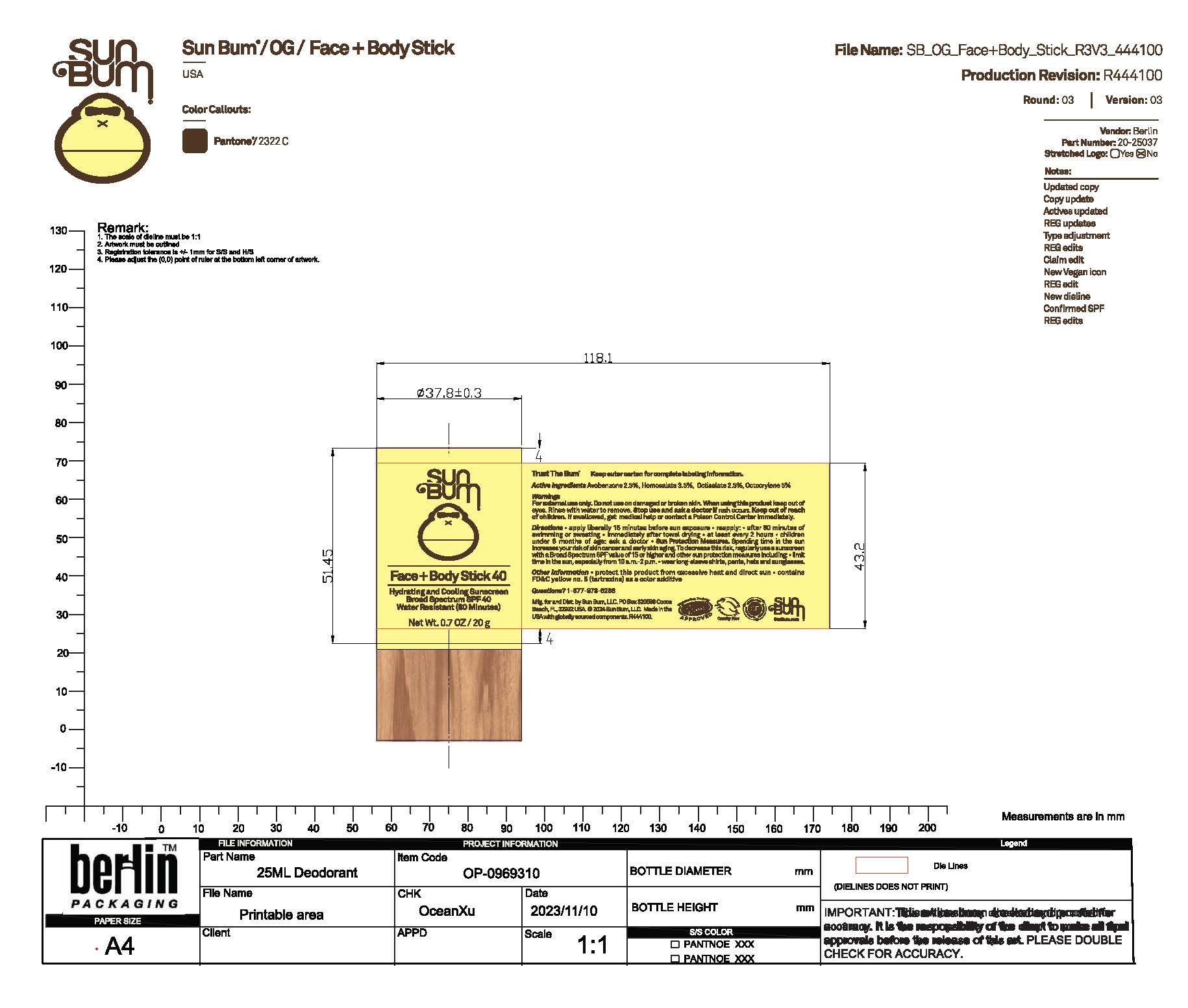 DRUG LABEL: Sun Bum Face and Body Stick 40
NDC: 69039-670 | Form: STICK
Manufacturer: Sun Bum, LLC
Category: otc | Type: HUMAN OTC DRUG LABEL
Date: 20251105

ACTIVE INGREDIENTS: HOMOSALATE 35 mg/1 g; AVOBENZONE 25 mg/1 g; OCTOCRYLENE 50 mg/1 g; OCTISALATE 25 mg/1 g
INACTIVE INGREDIENTS: SODIUM STEARATE; C18-38 ALKYL HYDROXYSTEAROYL STEARATE; WATER; BUTYLOCTYL SALICYLATE; VINYLPYRROLIDONE/HEXADECENE COPOLYMER; .ALPHA.-TOCOPHEROL ACETATE; FD&C YELLOW NO. 5; CANDELILLA WAX; PROPANEDIOL; PONGAMIA PINNATA SEED; GLYCERIN; CARTHAMUS TINCTORIUS SEED OLEOSOMES; ETHYLHEXYLGLYCERIN; SORBITAN OLIVATE; PHENOXYETHANOL

Sun Bum Face and Body Stick 40

Active ingredients

Avobenzone 2.5%, Homosalate 3.5%, Octisalate 2.5%, Octocrylene 5%

Purpose

Sunscreen

Uses

• helps prevent sunburn • if used as directed with other sun protection measures, (see Directions) decreases the risk of skin cancer and early skin aging caused by the sun

Warnings

For external use only

Do not use on damaged or broken skin

When using this product keep out of eyes. Rinse with water to remove.

Stop use and ask a doctor if rash occurs

Keep out of reach of children. If swallowed, get medical help or contact a Poison Control Center immediately.

Warnings

Keep Out Of Reach Of Children

Directions

• shake well before use

• apply liberally 15 minutes before sun exposure

• reapply: • after 80 minutes of swimming or sweating • immediately after towel drying • at least every 2 hours

• children under 6 months of age: ask a doctor

• Sun Protection Measures. Spending time in the sun increases your risk of skin cancer and early skin aging. To decrease this risk, regularly use a sunscreen with a Broad Spectrum SPF value of 15 or higher and other sun protection measures including:

• limit time in the sun, especially from 10 a.m.- 2 p.m.

• wear long-sleeved shirts, pants, hats and sunglasses

Directions

• apply liberally 15 minutes before sun exposure

• reapply: • after 80 minutes of swimming or sweating • immediately after towel drying • at least every 2 hours

• children under 6 months of age: ask a doctor

• Sun Protection Measures. Spending time in the sun increases your risk of skin cancer and early skin aging. To decrease this risk, regularly use a sunscreen with a Broad Spectrum SPF value of 15 or higher and other sun protection measures including:

• limit time in the sun, especially from 10 a.m.- 2 p.m.

• wear long-sleeved shirts, pants, hats and sunglasses

Other information

protect this product from excessive heat and direct sun

Inactive ingredients

water, carthamus tinctorius (safflower) oleosomes, sodium stearate, butyloctyl salicylate, euphorbia cerifera (candelilla) wax, propanediol, sorbitan olivate, VP/hexadecene copolymer, glycerin, fragrance, phenoxyethanol, C18-38 alkyl hydroxystearoyl stearate, pongamia pinnata seed extract, tocopheryl acetate, ethylhexylglycerin, yellow 5 lake

Questions

Questions? 1-877-978-6286